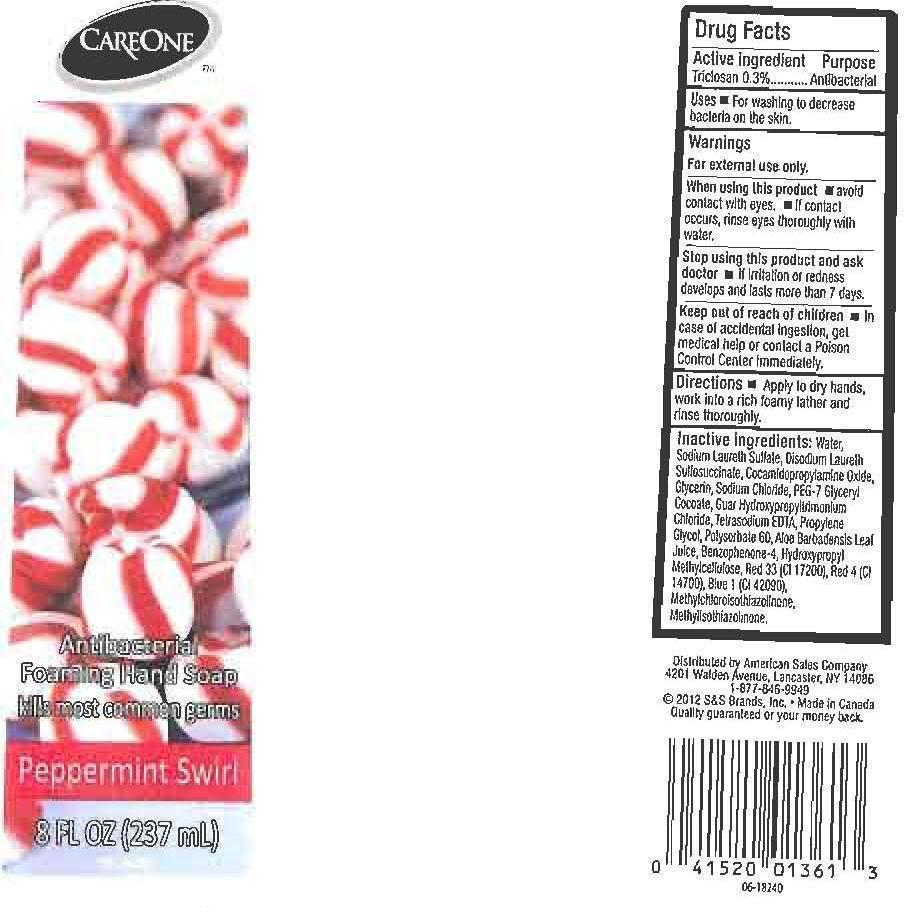 DRUG LABEL: CARE ONE
NDC: 41520-193 | Form: LIQUID
Manufacturer: AMERICAN SALES COMPANY
Category: otc | Type: HUMAN OTC DRUG LABEL
Date: 20120927

ACTIVE INGREDIENTS: TRICLOSAN 3 mg/1 mL
INACTIVE INGREDIENTS: WATER; SODIUM LAURETH SULFATE; DISODIUM LAURETH SULFOSUCCINATE; COCAMIDOPROPYLAMINE OXIDE; GLYCERIN; SODIUM CHLORIDE; PEG-7 GLYCERYL COCOATE; GUAR HYDROXYPROPYLTRIMONIUM CHLORIDE (1.7 SUBSTITUENTS PER SACCHARIDE); EDETATE SODIUM; PROPYLENE GLYCOL; POLYSORBATE 60; ALOE VERA LEAF; SULISOBENZONE; HYPROMELLOSES; D&C RED NO. 33; FD&C RED NO. 4; FD&C BLUE NO. 1; METHYLCHLOROISOTHIAZOLINONE; METHYLISOTHIAZOLINONE

DRUG FACTS

ACTIVE INGREDIENT

PURPOSE

ANTIBACTERIAL

USES

FOR WASHING TO DECREASE BACTERIA ON THE SKIN.

WARNINGS

FOR EXTERNAL USE ONLY.

WHEN USING THIS PRODUCT

STOP USING THIS PRODUCT AND ASK DOCTOR

KEEP OUT OF REACH OF CHILDREN

IN CASE OF ACCIDENTAL INGESTION, GET MEDICAL HELP OR CONTACT A POISON CONTROL CENTER IMMEDIATELY.

DIRECTIONS

APPLY TO DRY HANDS, WORK INTO A RICH FOAMY LATHER AND RINSE THOROUGHLY.

INACTIVE INGREDIENTS:

WATER (AQUA), SODIUM LAURETH SULFATE, DISODIUM LAURETH SULFOCCINATE, COCAMIDOPROPYLAMINE OXIDE, GLYCERIN, SODIUM CHLORIDE, PEG-7 GLYCERYL COCOATE, GUAR HYDROXYPROPYLTRIMONIUM CHLORIDE, TETRASODIUM EDTA, PROPYLENE GLYCOL, POLYSORBATE 60, ALOE BARBADENSIS LEAF JUICE, BENZOPHENONE-4, HYDROXYPROPYL METHYLCELLULOSE, RED 33 (CI 17200), RED 4 (CI 14700), BLUE 1 (CI 42090), METHYLCHLOROISOTHIAZOLINONE, METHYLISOTHIAZOLINONE.